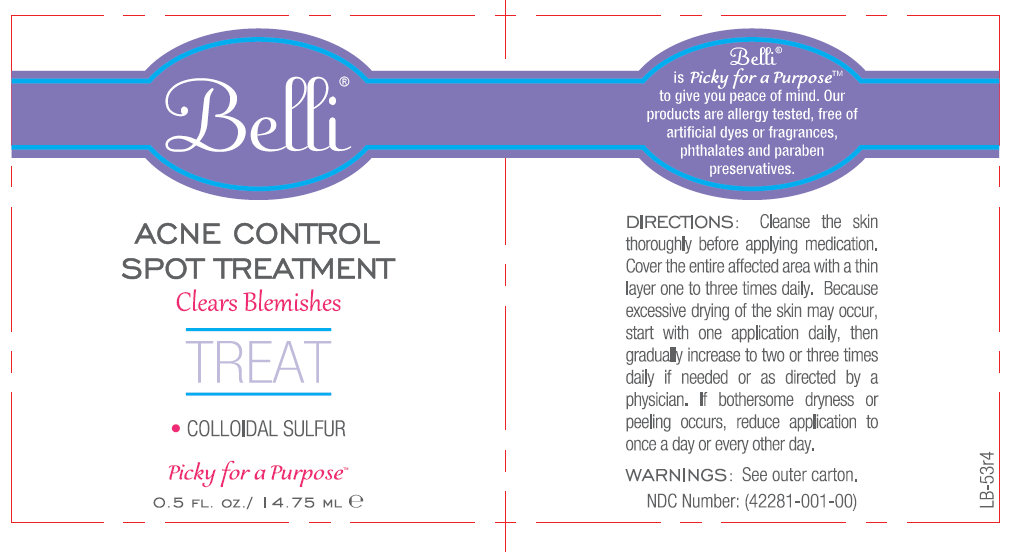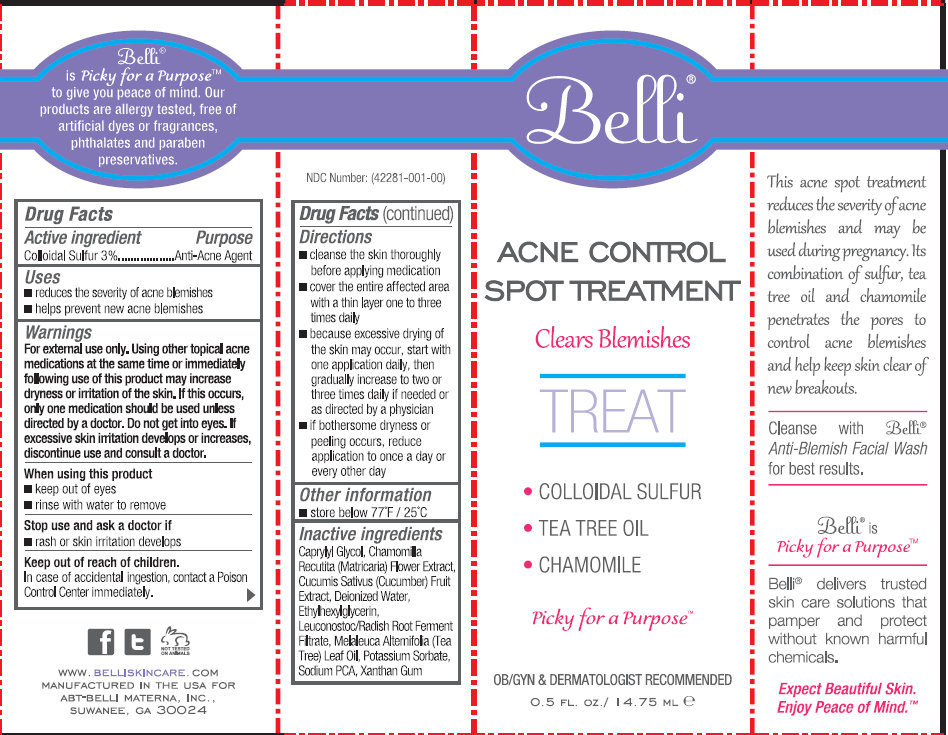 DRUG LABEL: Belli Acne Control Spot Treatment
NDC: 42281-001 | Form: CREAM
Manufacturer: BODY HALO LLC
Category: otc | Type: HUMAN OTC DRUG LABEL
Date: 20250129

ACTIVE INGREDIENTS: SULFUR 30 mg/1 mL
INACTIVE INGREDIENTS: CAPRYLYL GLYCOL; CHAMOMILE; CUCUMBER; WATER; ETHYLHEXYLGLYCERIN; RADISH; TEA TREE OIL; POTASSIUM SORBATE; SODIUM PYRROLIDONE CARBOXYLATE; XANTHAN GUM

BODY HALO - Belli - Acne Control Spot Treatment (42281-001)

Active ingredient

Colloidal Sulfur 3%

Purpose

Anti-Acne Agent

Uses

- reduces the severity of acne blemishes
- helps prevent new acne blemishes

Warnings

For external use only. Using other topical acne medications at the same time or immediately following use of this product may increase dryness or irritation of the skin. If this occurs, only one medication should be used unless directed by a doctor. Do not get into eyes. If excessive skin irritation develops or increases, discontinue use and consult a doctor.

When using this product

- keep out of eyes
- rinse with water to remove

Stop use and ask a doctor if

- rash or skin irritation develops

Keep out of reach of children

In case of accidental ingestion, contact a Poison Control Center immediately.

Directions

- cleanse the skin thoroughly before applying medication
- cover the entire affected area with a thin layer one to three times daily
- because excessive drying of the skin may occur, start with one application daily, then gradually increase to two or three times daily if needed or as directed by a physician
- if bothersome dryness or peeling occurs, reduce application to once a day or every other day

Other information

- store below 77 degrees F / 25 degrees C

Inactive ingredients

Caprylyl Glycol, Chamomilla Recutita (Matricaria) Flower Extract, Cucumis Sativus (Cucumber) Fruit Extract, Deionized Water, Ethylhexylglycerin, Leuconostoc/Radish Root Ferment Filtrate, Melaleuca Alternifolia (Tea Tree) Leaf Oil, Potassium Sorbate, Sodium PCA, Xanthan Gum